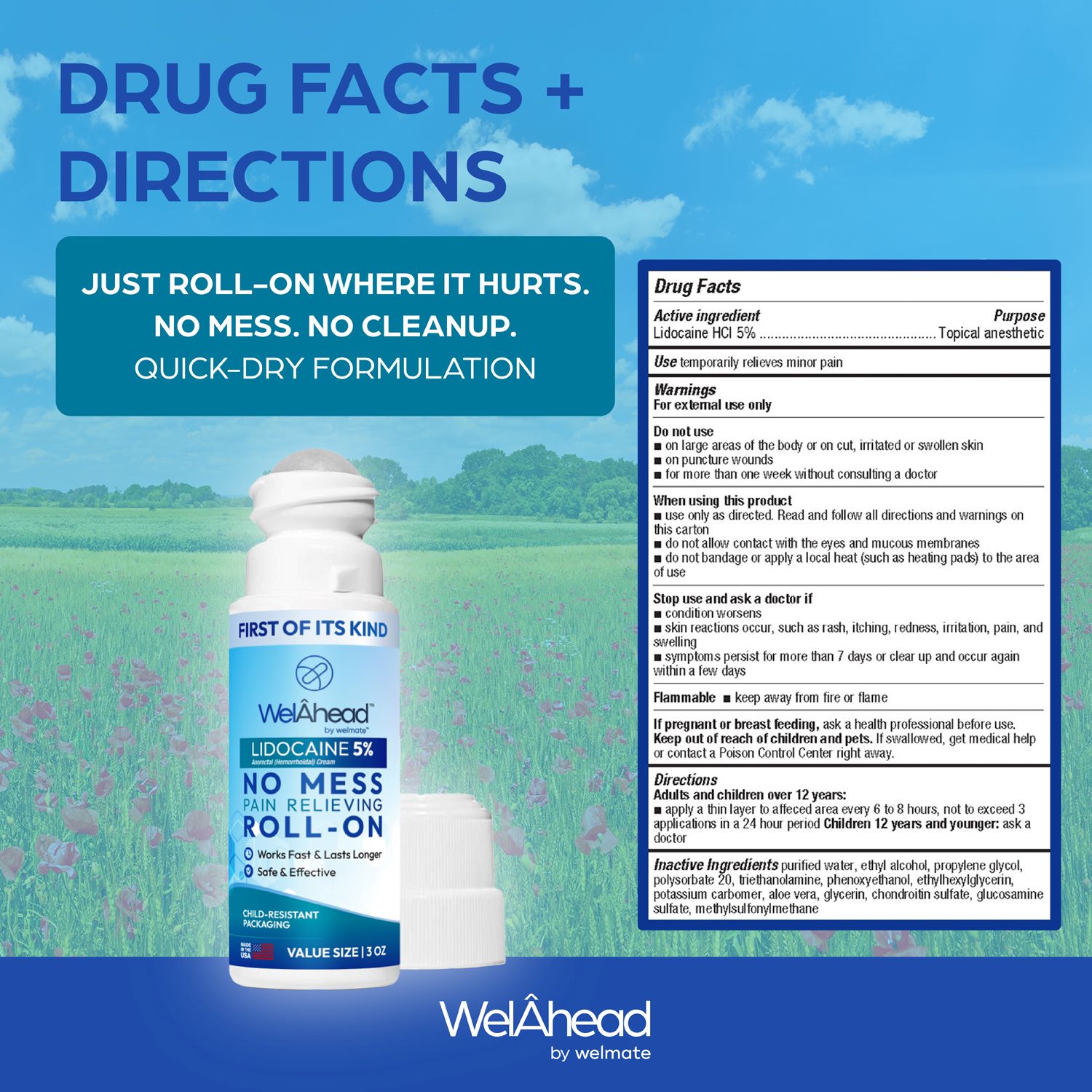 DRUG LABEL: WelAhead by Welmate Lidocaine 5% Roll-on
NDC: 83833-101 | Form: SOLUTION
Manufacturer: OTC PHARM LLC
Category: otc | Type: HUMAN OTC DRUG LABEL
Date: 20250521

ACTIVE INGREDIENTS: LIDOCAINE HYDROCHLORIDE ANHYDROUS 5 g/100 mL
INACTIVE INGREDIENTS: CHONDROITIN SULFATE (BOVINE); WATER; ALOE VERA LEAF; ETHYLHEXYLGLYCERIN; GLUCOSAMINE SULFATE; GLYCERIN; ALCOHOL; DIMETHYL SULFONE; POLYSORBATE 20; TROLAMINE; PHENOXYETHANOL; POTASSIUM CARBONATE; PROPYLENE GLYCOL

WelAhead by Welmate Lidocaine 5% Roll-on 83833-101

Active Ingredient

Lidocaine HCl 5%

Purporse

Topical Analgesic

Use

Temporarily Relieves minor pain

Warnings

For external use only

Do not use

- on large areas of the body or on cut, irritated or swollen skin
- on puncture wounds
- for more than week without consulting a doctor

When using this product:

- use cnly as directed. Read and follow all directions and warnings on this carton
- do not allow contact with the eyes and mucous membranes
- do not bandage or apply a local heat (such as heating pads) to the area of use

Stop use and aska doctor if

- condition worsens
- skin reactions occur, such as rash, itching, redness, irritation, pain, and swelling
- symptoms persist for more than 7 days or clear up and occur again within a days

Flammable

- keep away from fire or flame

If pregnant or breast freding, ask a health professional before use.

Keep out of reach of children and pets. If swallowed, get medical help or contact a Poison Control Center right away.

Directions

Adults and children over 12 years:

apply a thin layer to affeced area every 6 to 8 hours, not to exceed 3 applications in a 24 hour period

Children 12 years and younger: ask a doctor

Inactive Ingrediants

purified water, ethyl alcohol, propylene glycol, polysorbate 20, triethanolamine, phenoxyethanol, ethylhexylglycerin,

potassium carbomer, aloe vera, glycerin, chonüoitin sulfate, glucosamine sulfate, methylsulfonylmethane